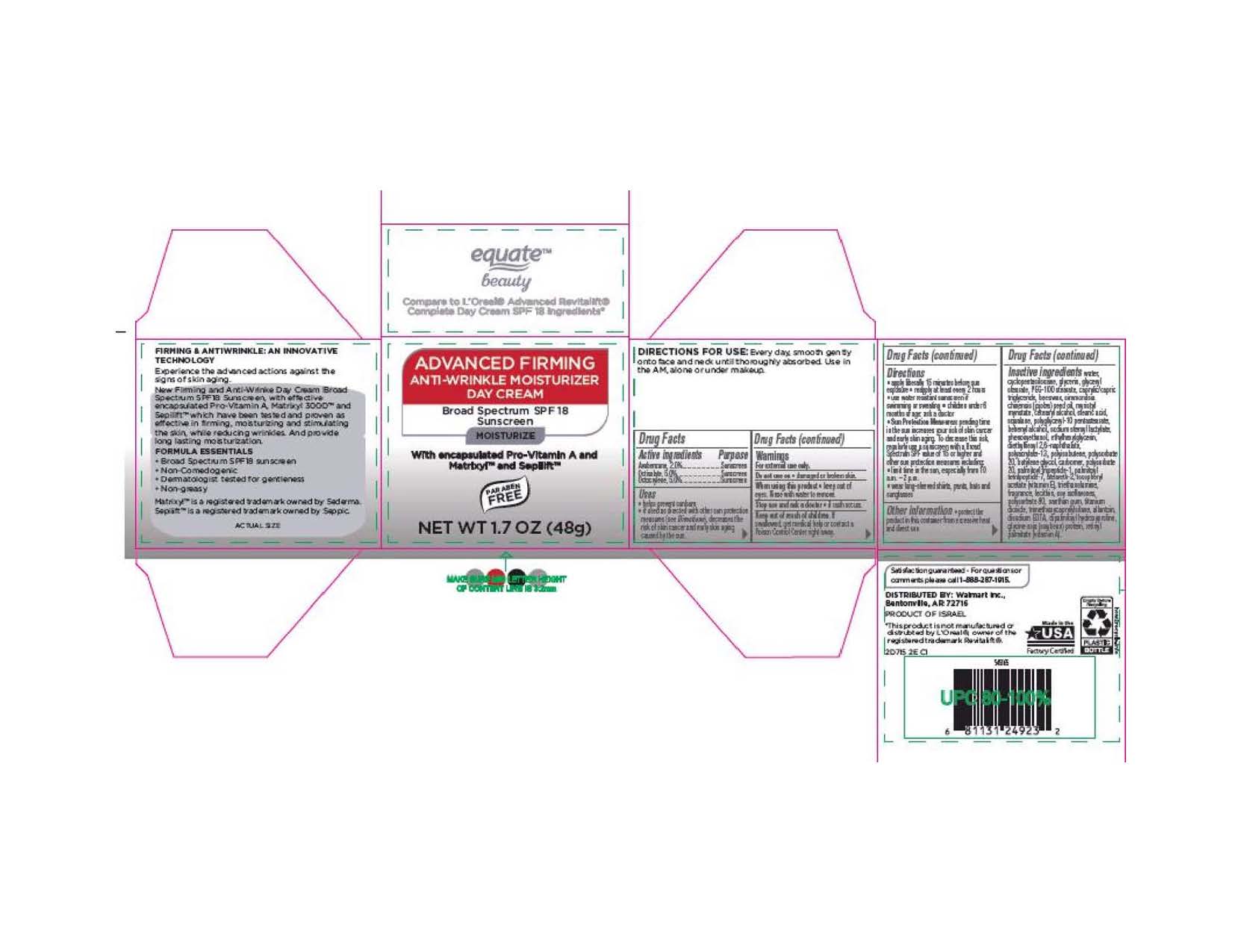 DRUG LABEL: Equate
NDC: 49035-818 | Form: CREAM
Manufacturer: Wal-Mart Stores, Inc.
Category: otc | Type: HUMAN OTC DRUG LABEL
Date: 20180510

ACTIVE INGREDIENTS: AVOBENZONE .96 g/48 g; OCTISALATE 2.41 g/48 g; OCTOCRYLENE 2.41 g/48 g
INACTIVE INGREDIENTS: WATER; CYCLOMETHICONE 5; GLYCERIN; GLYCERYL MONOSTEARATE; PEG-100 STEARATE; MEDIUM-CHAIN TRIGLYCERIDES; YELLOW WAX; JOJOBA OIL; MYRISTYL MYRISTATE; CETOSTEARYL ALCOHOL; STEARIC ACID; SQUALANE; POLYGLYCERYL-10 PENTASTEARATE; DOCOSANOL; SODIUM STEAROYL LACTYLATE; PHENOXYETHANOL; ETHYLHEXYLGLYCERIN; DIETHYLHEXYL 2,6-NAPHTHALATE; SODIUM ACRYLATE; POLYISOBUTYLENE (1300 MW); POLYSORBATE 20; BUTYLENE GLYCOL; CARBOMER 940; PALMITOYL TRIPEPTIDE-1; PALMITOYL TETRAPEPTIDE-7; STEARETH-2; .ALPHA.-TOCOPHEROL ACETATE; TROLAMINE; LECITHIN, SOYBEAN; SOY ISOFLAVONES; POLYSORBATE 80; XANTHAN GUM; TITANIUM DIOXIDE; TRIMETHOXYCAPRYLYLSILANE; ALLANTOIN; EDETATE DISODIUM ANHYDROUS; DIPALMITOYL HYDROXYPROLINE; SOY PROTEIN; VITAMIN A PALMITATE

Active Ingredients:

Avobenzone, 2%

Octisalate, 5%

Octocrylene, 5%

Purpose

Sunscreen

Sunscreen

Sunscreen

Uses

•helps prevent sunburn

•if used as directed with other sun protection measures

(see Directions), decreases the risk of skin cancer and

early skin aging caused by the sun.

Warnings

For external use only.

Do not use on •damaged or broken skin

When using this product •keep out of eyes. Rinse with

water to remove.

Stop use and ask a doctor •if rash occurs

Keep out of reach of children. If swallowed, get medical

help or contact a Poison Control Center right away.

DOSAGE AND ADMINISTRATION

Directions •apply liberally 15 minutes before sun

exposure •reapply at least every 2 hours •use water

resistant sunscrenn if swimming or sweating •children

under 6 months of age: ask a doctor

•Sun Protection Measures: Spending time in the sun increases your risk

of skin cancer and early skin aging. To decrease this risk,

regularly use a sunscreen with a Broad SpectrumSPF

value of 15 or higher and other sun protection measures

including

•limit time in the sun, especially from 10 a.m.

- 2 p.m.

•wear long-sleeved shirts, pants, hats and

sunglasses.

Other information •protect the product in this

container from excessive heat and direct sun.

INACTIVE INGREDIENT

Inactive ingredients Water, Cyclopentasiloxane, Glycerin, Glyceryl Stearate,

PEG-100 Stearate, Caprylic/Capric Triglyceride, Beeswax, Simmondsia Chinensis (Jojoba) Seed Oil,

Myristyl Myristate, Cetearyl Alcohol, Stearic Acid, Squalane, Polyglyceryl-10 Pentastearate,

Behenyl Alcohol, Sodium Steroyl Lactylate, Phenoxyethanol, Ethylhexylglycerin,

Diethylhexyl 2,6-Naphthalate, Polyacrylate-13, Polyisobutene, Polysorbate 20,

Butylene Glycol, Carbomer, Palmitoyl Tripeptide-1, Palmitoyl Tetrapeptide-7,

Steareth-2, Tocopheryl Acetate (Vitamin E), Triethanolamine, Fragrance,

Lecithin, Soy Isoflavones, Polysorbate 80, Xanthan Gum, Titanium Dioxide,

Trimethoxycaprylylsilane, Allantoin, Disodium EDTA, Dipalmitoyl Hydroxyproline,

Glycine Soja (Soybean) Protein, Retinyl Palmitate (Vitamin A).